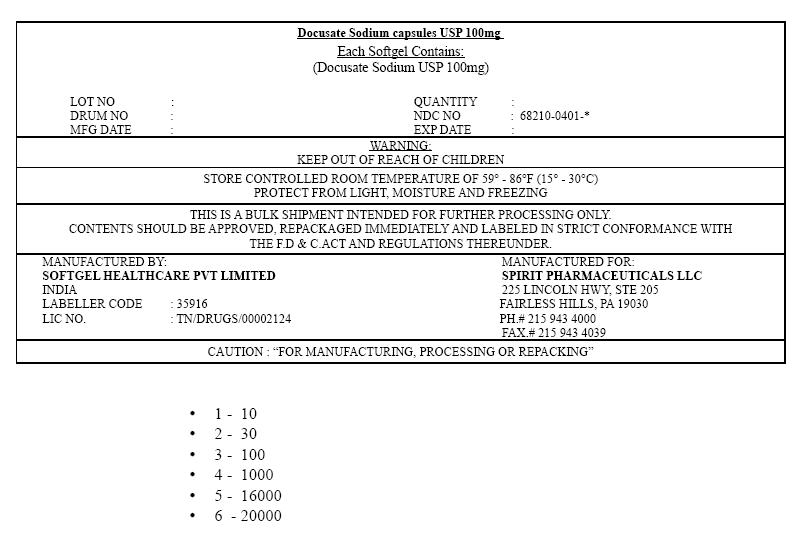 DRUG LABEL: DOCUSATE SODIUM
NDC: 68210-0401 | Form: CAPSULE, LIQUID FILLED
Manufacturer: SPIRIT PHARMACEUTICALS,LLC
Category: otc | Type: HUMAN OTC DRUG LABEL
Date: 20100209

ACTIVE INGREDIENTS: DOCUSATE SODIUM 100 mg/1 1
INACTIVE INGREDIENTS: POLYETHYLENE GLYCOL 400; GLYCERIN; GELATIN; SORBITOL; WATER; D&C RED No. 33; FD&C RED No. 40; FD&C Yellow No. 6

Docusate Sodium capsules USP 100mg

Drug Facts

Active ingredient (in each capsule)

Docusate sodium 100 mg

Purpose

Stool softener

Uses

- relieves occasional constipation (irregularity)
- generally produces bowel movement in 12 to 72 hours

Warnings

Do not use

- if you are presently taking mineral oil, unless told to do so by a doctor

Ask a doctor before use if you have

- stomach pain
- nausea
- vomiting
- noticed a sudden change in bowel habits that lasts over 2 weeks

Stop use and ask a doctor if

- you have rectal bleeding or fail to have a bowel movement after use of a laxative. These could be signs of a serious condition.
- you need to use a laxative for more than 1 week

PREGNANCY OR BREAST FEEDING

If pregnant or breast-feeding, ask a health professional before use.

Keep out of reach of children. In case of overdose, get medical help or contact a Poison Control Center right away.

Directions

- Take only by mouth. Doses may be taken as a single daily dose or in divided doses.

adults and children 12 years and over | take 1-3 capsules daily
children 2 to under 12 years of age | take 1 capsule daily
children under 2 years | ask a doctor

Inactive ingredients

D&C Red No. 33, FD&C Red No. 40, FD&C Yellow No. 6, gelatin, glycerin, methylparaben, PEG 400, propylene glycol, propylparaben, sorbitol, titanium dioxide

PRINCIPAL DISPLAY PANEL

Docusate Sodium capsules USP 100mg

Each Softgel Contains:
(Docusate Sodium USP 100mg)

LOT NO | : |  |  | QUANTITY | :
DRUM NO | : |  |  | NDC NO | : 68210-0401-*
MFG DATE | : |  |  | EXP DATE | :

WARNING:
KEEP OUT OF REACH OF CHILDREN

STORE CONTROLLED ROOM TEMPERATURE OF 59° – 86°F (15° – 30°C)
PROTECT FROM LIGHT, MOISTURE AND FREEZING

THIS IS A BULK SHIPMENT INTENDED FOR FURTHER PROCESSING ONLY.
CONTENTS SHOULD BE APPROVED, REPACKAGED IMMEDIATELY AND LABELED IN STRICT CONFORMANCE WITH
THE F.D & C.ACT AND REGULATIONS THEREUNDER.

MANUFACTURED BY:
SOFTGEL HEALTHCARE PVT LIMITED
INDIA
LABELLER CODE : 35916
LIC NO. : TN/DRUGS/00002124

MANUFACTURED FOR:
SPIRIT PHARMACEUTICALS LLC
225 LINCOLN HWY, STE 205
FAIRLESS HILLS, PA 19030
PH.# 215 943 4000
FAX.# 215 943 4039

CAUTION : "FOR MANUFACTURING, PROCESSING OR REPACKING"

- 1 - 10
- 2 - 30
- 3 - 100
- 4 - 1000
- 5 - 16000
- 6 - 20000